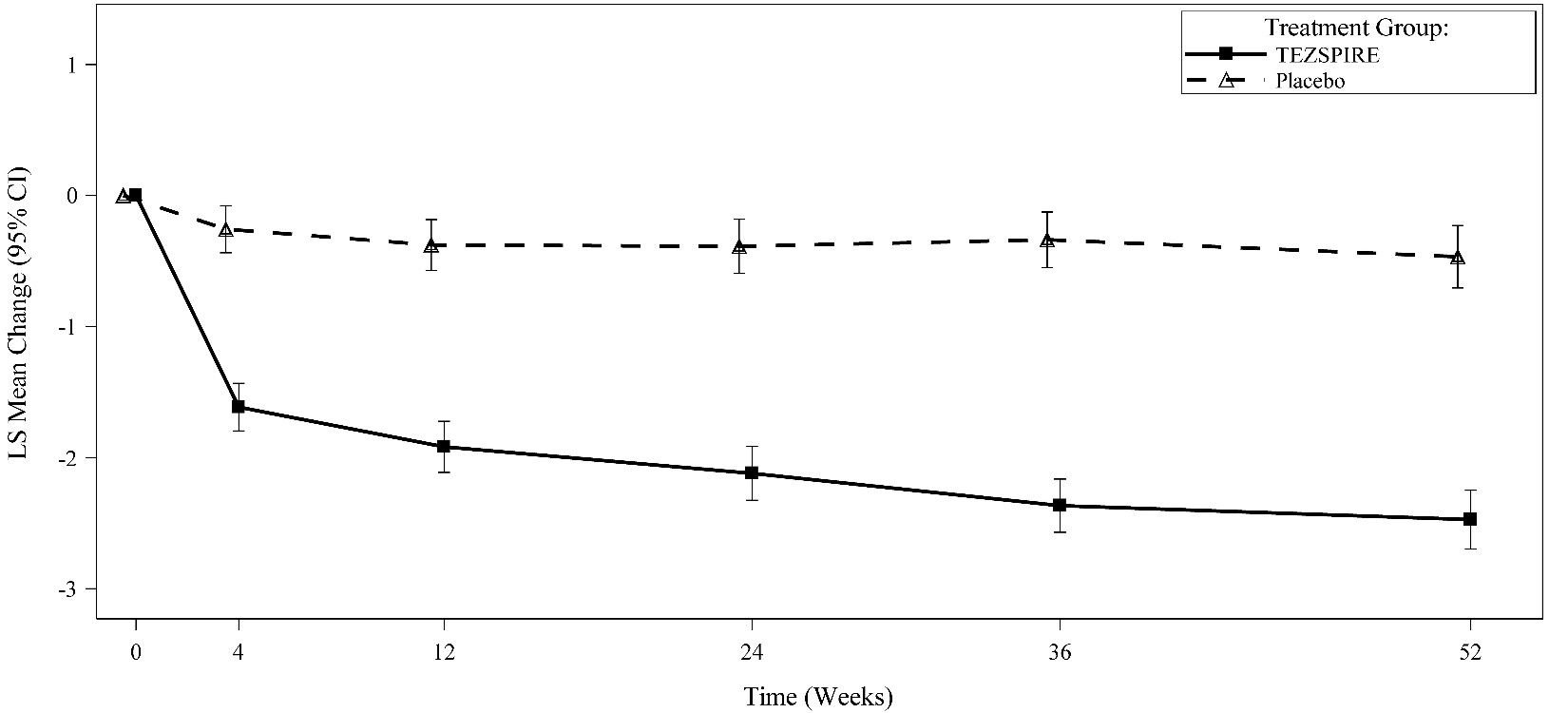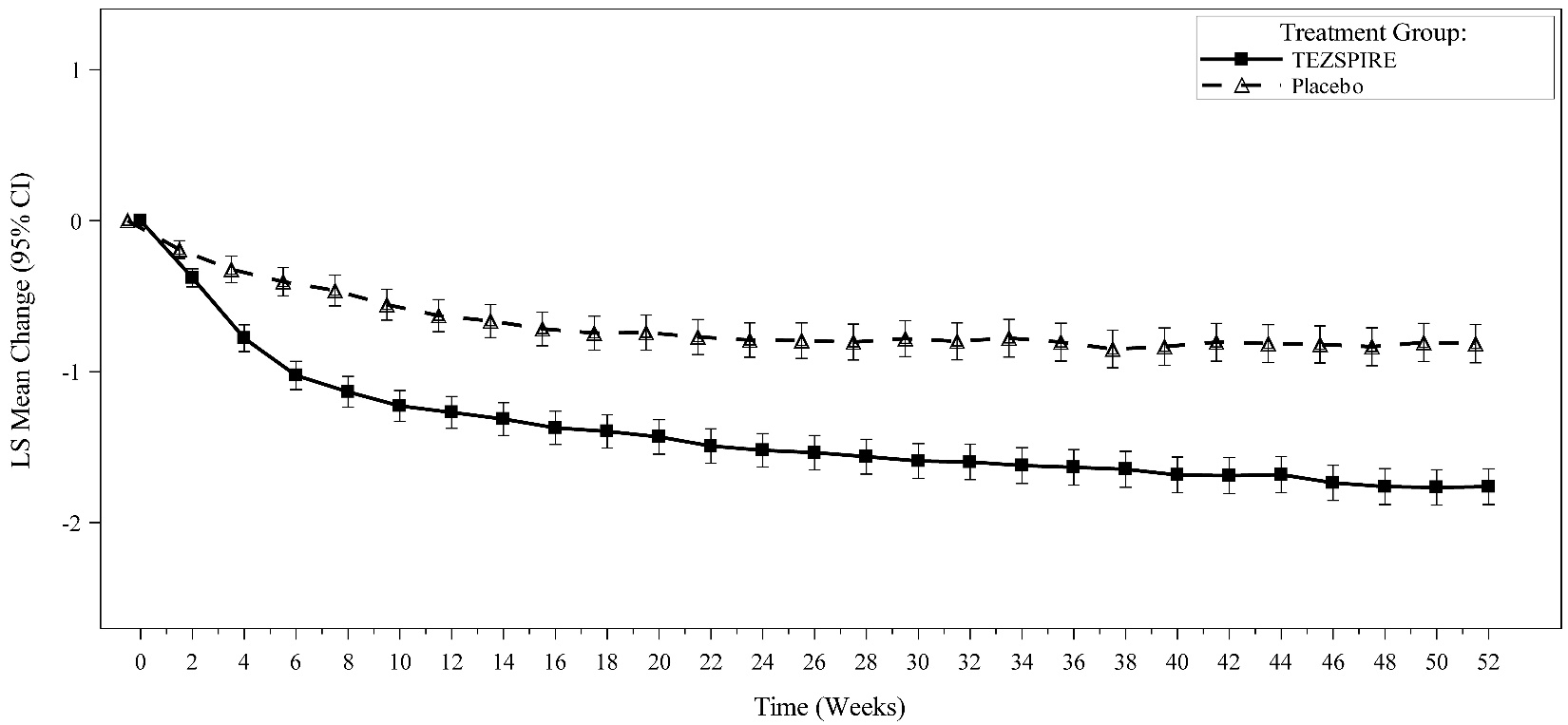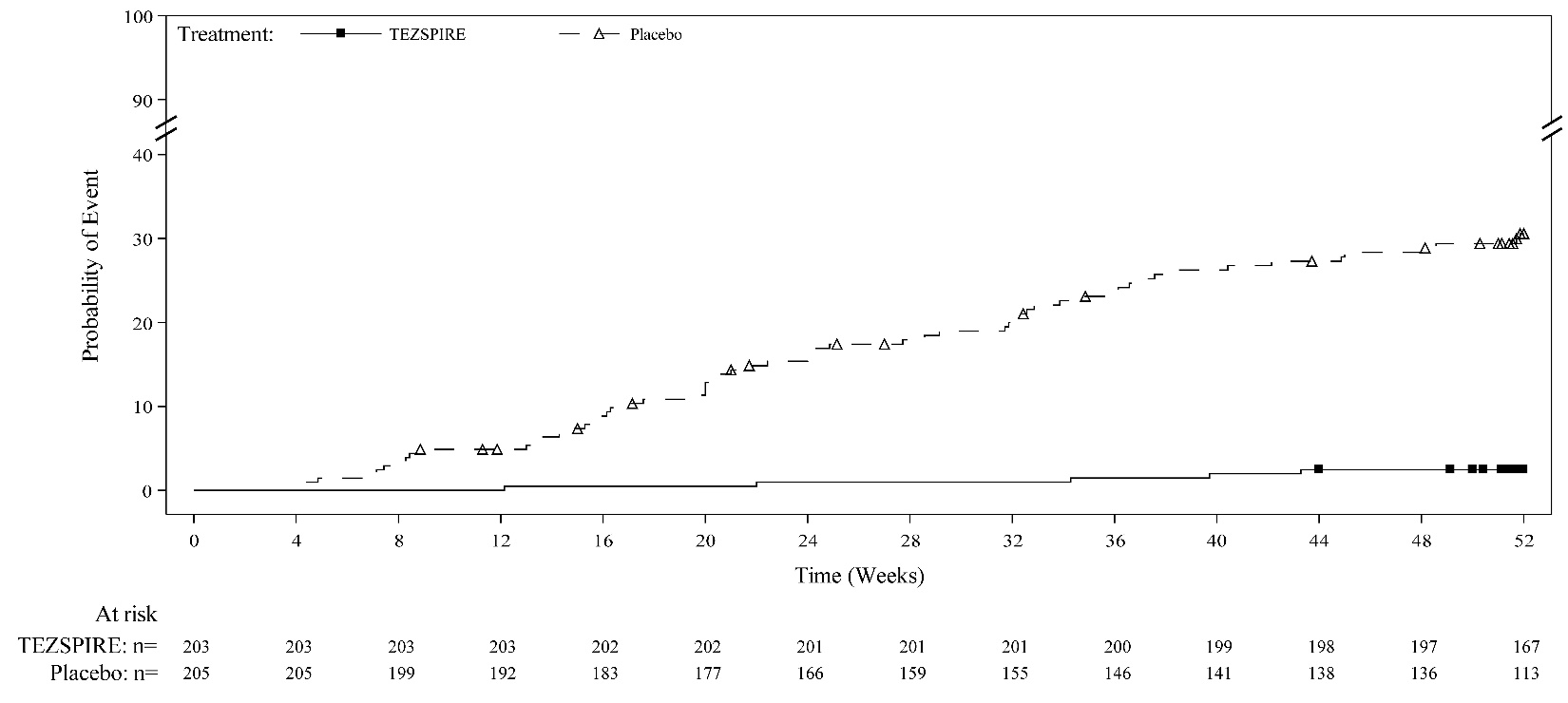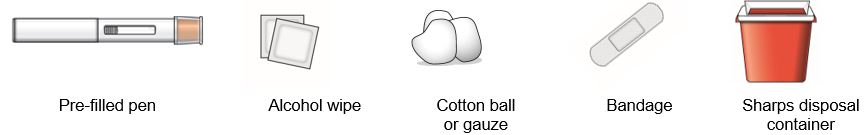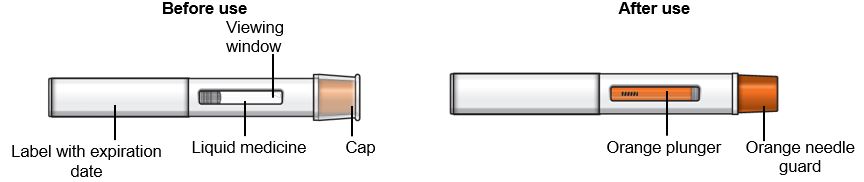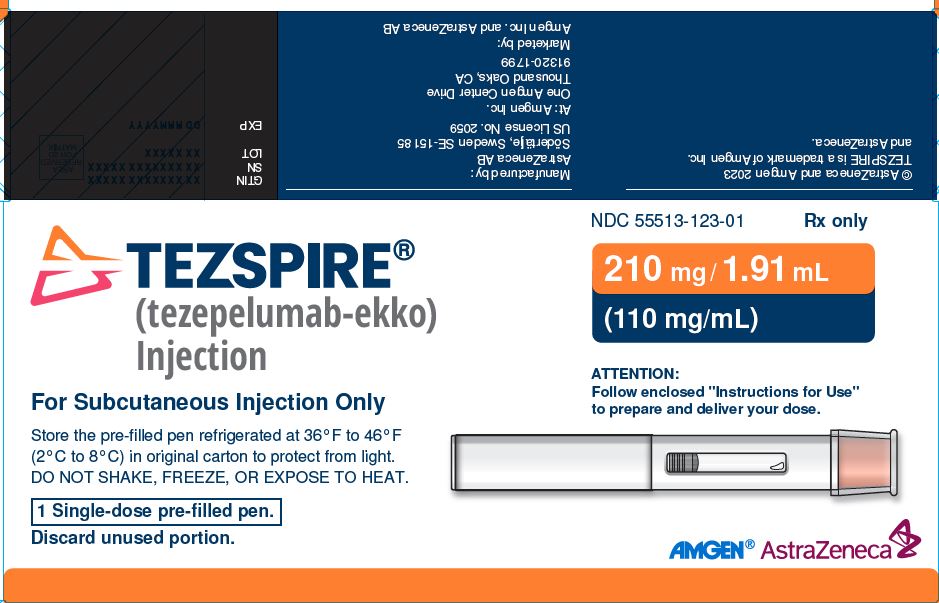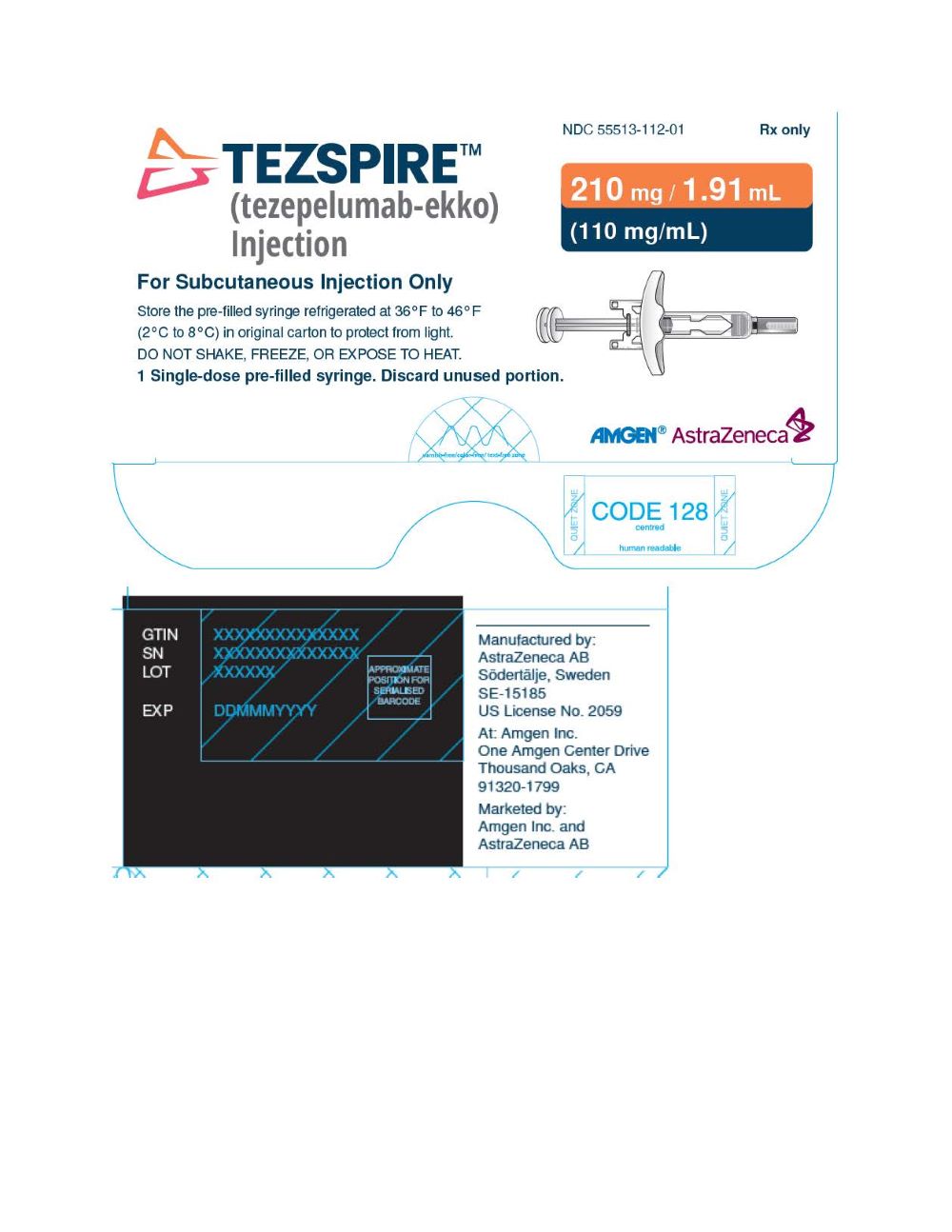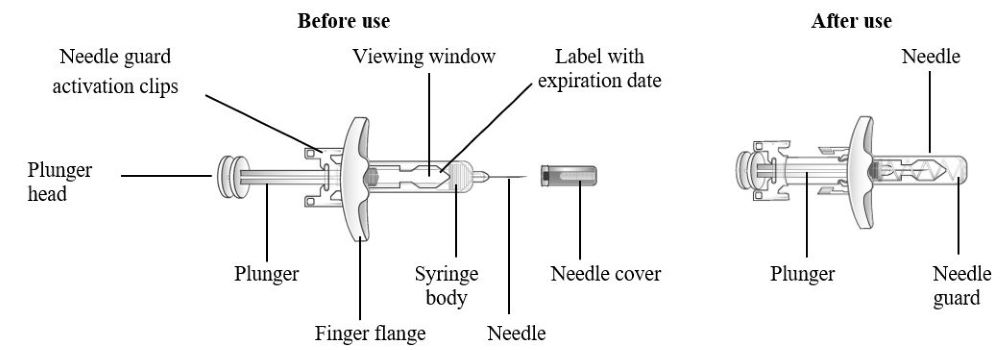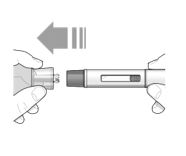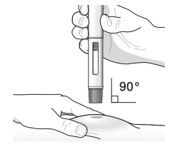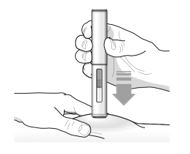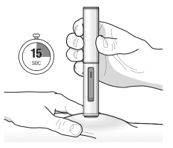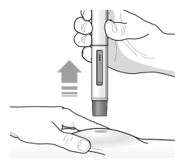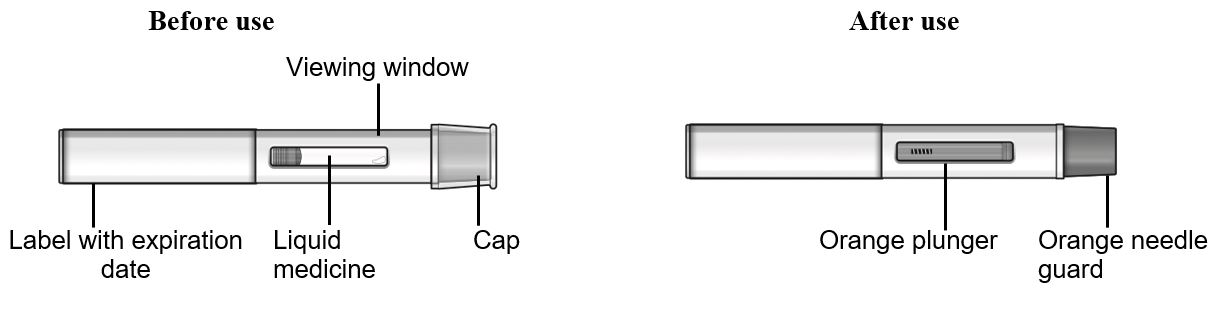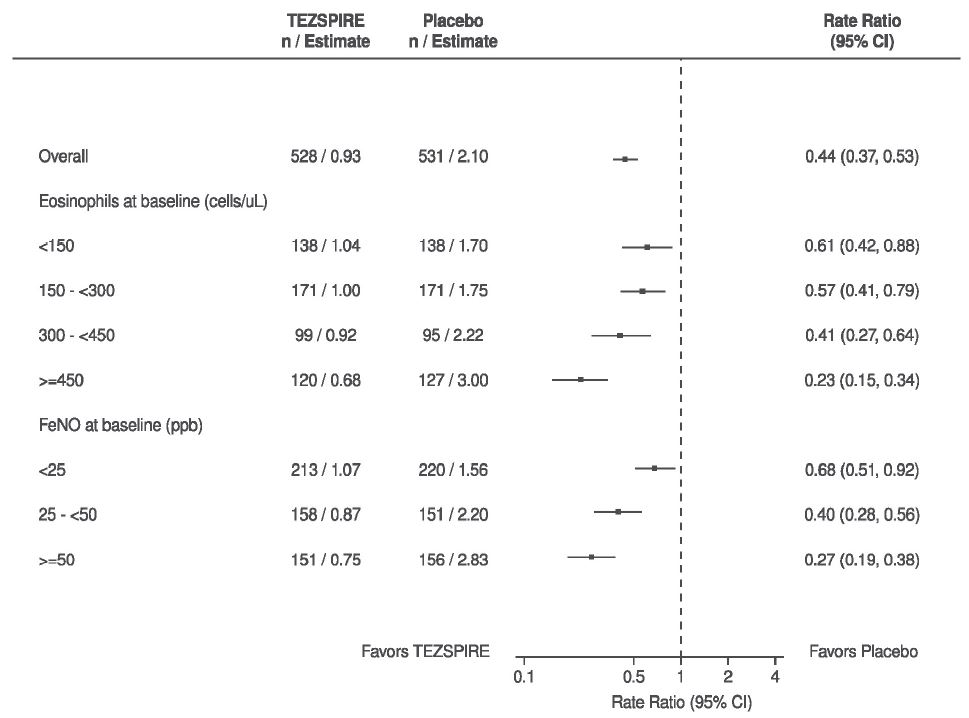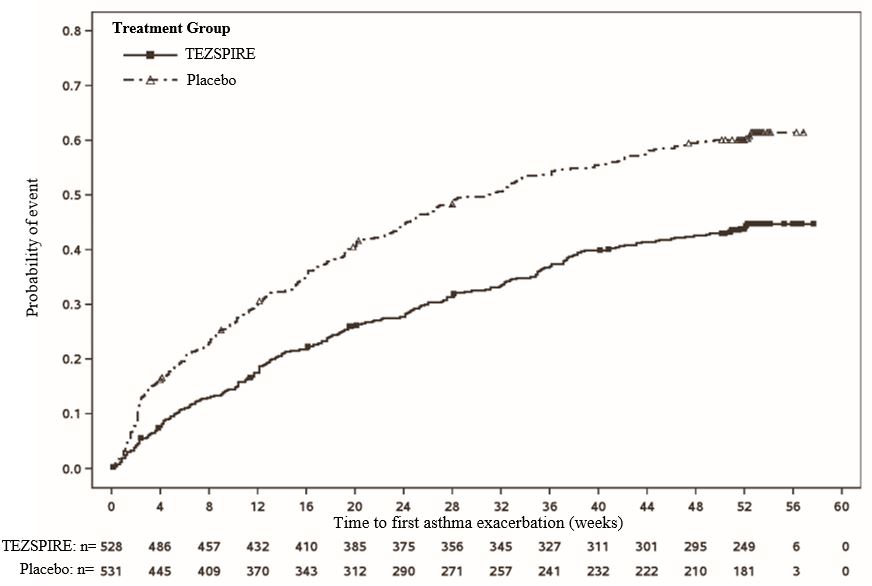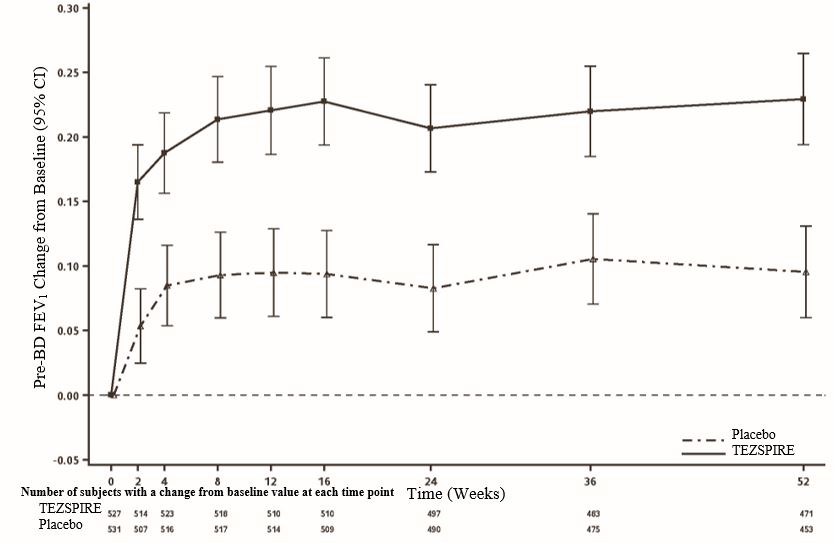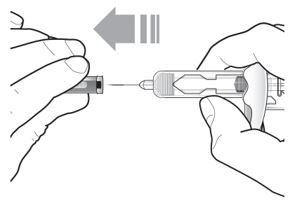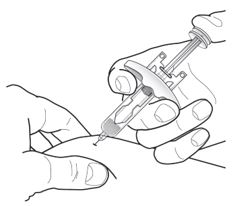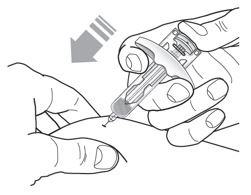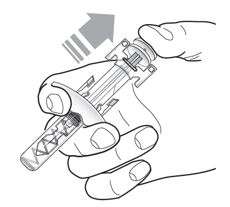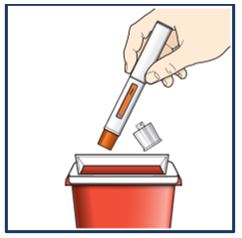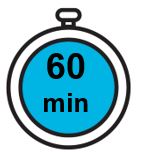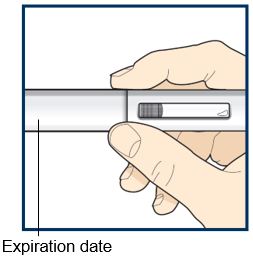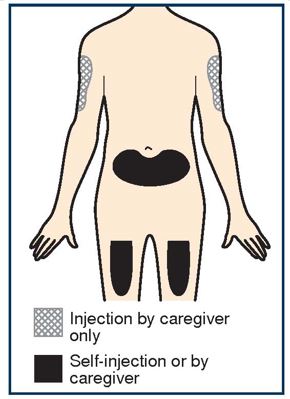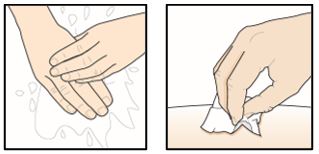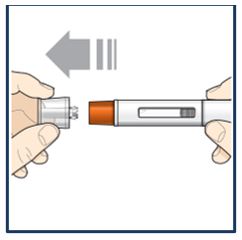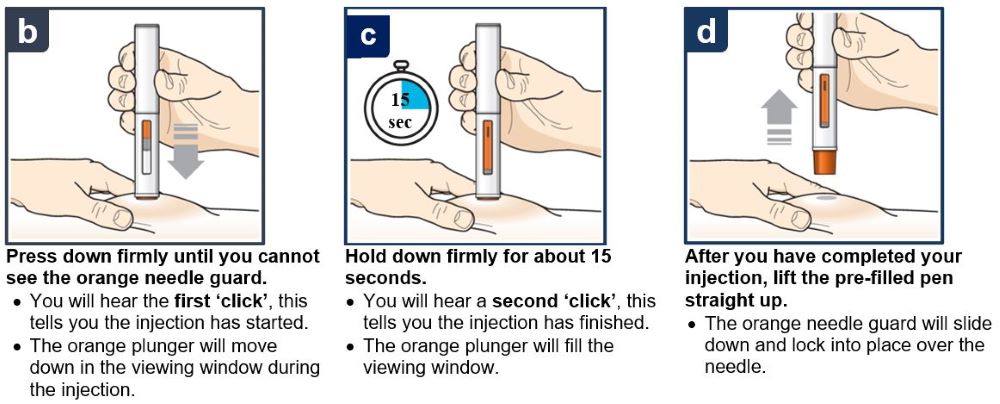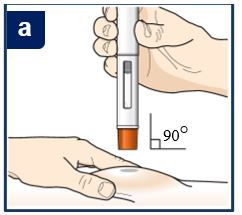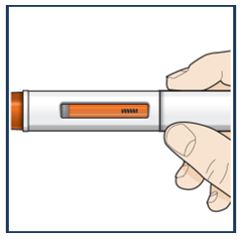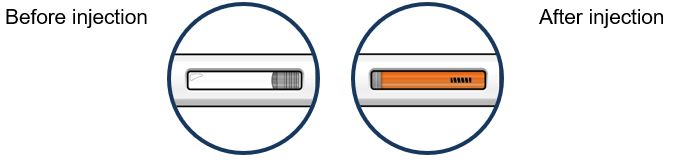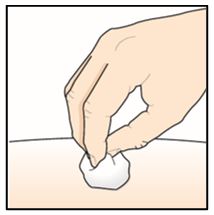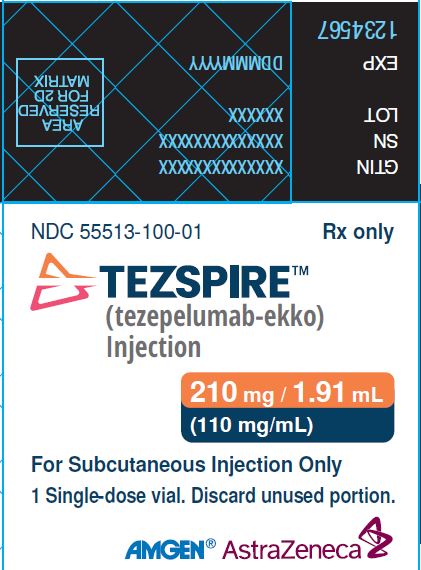 DRUG LABEL: TEZSPIRE
NDC: 55513-100 | Form: INJECTION, SOLUTION
Manufacturer: Amgen Inc
Category: prescription | Type: HUMAN PRESCRIPTION DRUG LABEL
Date: 20251017

ACTIVE INGREDIENTS: TEZEPELUMAB 210 mg/1.9 mL
INACTIVE INGREDIENTS: PROLINE; ACETIC ACID; POLYSORBATE 80; SODIUM HYDROXIDE; WATER

HIGHLIGHTS OF PRESCRIBING INFORMATION

These highlights do not include all the information needed to use TEZSPIRE safely and effectively. See full prescribing information for TEZSPIRE.
TEZSPIRE® (tezepelumab-ekko) injection, for subcutaneous use
Initial U.S. Approval: 2021

RECENT MAJOR CHANGES

Indications and Usage (1.2) 10/2025

1 INDICATIONS AND USAGE

TEZSPIRE is a thymic stromal lymphopoietin (TSLP) blocker, human monoclonal antibody (IgG2λ), indicated:

- for the add-on maintenance treatment of adult and pediatric patients aged 12 years and older with severe asthma. (1.1)
Limitations of Use:
Not for relief of acute bronchospasm or status asthmaticus. (1.1)
- for the add-on maintenance treatment of adult and pediatric patients aged 12 years and older with inadequately controlled chronic rhinosinusitis with nasal polyps (CRSwNP). (1.2)

2 DOSAGE AND ADMINISTRATION

Recommended dosage is 210 mg administered once every 4 weeks. (2.1)

- Administer by subcutaneous injection. (2.1)
- See full prescribing information for preparation and administration instructions. (2.2)

3 DOSAGE FORMS AND STRENGTHS

Injection:

- 210 mg/1.91 mL (110 mg/mL) solution in a single-dose glass vial. (3)
- 210 mg/1.91 mL (110 mg/mL) solution in a single-dose pre-filled syringe. (3)
- 210 mg/1.91 mL (110 mg/mL) solution in a single‑dose pre‑filled pen. (3)

4 CONTRAINDICATIONS

Known hypersensitivity to tezepelumab-ekko or excipients. (4)

5 WARNINGS AND PRECAUTIONS

- Hypersensitivity Reactions: Hypersensitivity reactions have been observed in the clinical trials (e.g., rash, allergic conjunctivitis) following the administration of TEZSPIRE. Postmarketing cases of anaphylaxis have been reported. Initiate appropriate treatment as clinically indicated in the event of a hypersensitivity reaction. (5.1)
- Risk Associated with Abrupt Reduction in Corticosteroid Dosage: Do not discontinue systemic or inhaled corticosteroids abruptly upon initiation of therapy with TEZSPIRE. Decrease corticosteroids gradually, if appropriate. (5.3)
- Parasitic (Helminth) Infection: Treat patients with pre-existing helminth infections before therapy with TEZSPIRE. If patients become infected while receiving TEZSPIRE and do not respond to anti-helminth treatment, discontinue TEZSPIRE until the parasitic infection resolves. (5.4)
- Vaccination: Avoid use of live attenuated vaccines. (5.5)

6 ADVERSE REACTIONS

Most common adverse reactions (incidence ≥ 3%) are:

- Asthma: pharyngitis, arthralgia, and back pain. (6.1)
- Chronic rhinosinusitis with nasal polyps: nasopharyngitis, upper respiratory tract infection, epistaxis, pharyngitis, back pain, influenza, injection site reaction and arthralgia. (6.1)

To report SUSPECTED ADVERSE REACTIONS, contact AstraZeneca at 1-800-236-9933 or FDA at 1-800-FDA-1088 or www.fda.gov/medwatch.

FULL PRESCRIBING INFORMATION

1 INDICATIONS AND USAGE

1.1 Asthma

TEZSPIRE is indicated for the add-on maintenance treatment of adult and pediatric patients aged 12 years and older with severe asthma.

Limitations of Use:

TEZSPIRE is not indicated for the relief of acute bronchospasm or status asthmaticus.

1.2 Chronic Rhinosinusitis with Nasal Polyps

TEZSPIRE is indicated for the add-on maintenance treatment of adult and pediatric patients aged 12 years and older with inadequately controlled chronic rhinosinusitis with nasal polyps (CRSwNP).

2 DOSAGE AND ADMINISTRATION

2.1 Recommended Dosage

The recommended dosage of TEZSPIRE is 210 mg administered subcutaneously once every 4 weeks.

Missed Dose Information

If a dose is missed, administer the dose as soon as possible. Thereafter, the patient can continue (resume) dosing on the usual day of administration. If the next dose is already due, then administer as planned.

2.2 Preparation and Administration Instructions

TEZSPIRE vial and pre‑filled syringe are intended for administration by a healthcare provider.

TEZSPIRE pre-filled pen can be administered by patients/caregivers or healthcare providers. Patients/caregivers may administer TEZSPIRE pre-filled pen after proper training in subcutaneous injection technique and after the healthcare provider determines it is appropriate.

Each vial, pre-filled syringe and pre‑filled pen contain a single dose of TEZSPIRE.

- Prior to administration, remove TEZSPIRE from the refrigerator and allow it to reach room temperature. This generally takes 60 minutes. Do not expose to heat and do not shake. Do not use if the security seal on the carton has been broken. Do not put back in the refrigerator once TEZSPIRE has reached room temperature.
- Visually inspect TEZSPIRE for particulate matter and discoloration prior to administration. TEZSPIRE is a clear to opalescent, colorless to light yellow solution. Do not use TEZSPIRE if liquid is cloudy, discolored, or if it contains large particles or foreign particulate matter. Do not use if the vial, pre-filled syringe or pre‑filled pen has been dropped or damaged or if the expiration date has passed.
- Inject TEZSPIRE 210 mg (contents of one vial, one pre-filled syringe or one pre-filled pen as described below) subcutaneously into the thigh or abdomen, except for the 2 inches (5 cm) around the navel. If a healthcare provider or caregiver administers the injection, the upper arm can also be used. A patient should not self-inject in the upper arm. TEZSPIRE should not be injected into areas where the skin is tender, bruised, erythematous, or hardened. It is recommended to rotate the injection site with each injection.

Administration Instructions for Single-Dose Pre-filled Syringe

Refer to Figure 1 to identify the pre-filled syringe components for use in the administration steps.

Do not remove the needle cover until Step 2 of these instructions when you are ready to inject TEZSPIRE. Do not touch the needle guard activation clips to prevent premature activation of the needle safety guard.

Figure 1 TEZSPIRE Pre-filled Syringe Components

1. | Grasp the syringe body to remove the pre-filled syringe from its carton. Do not grab the pre-filled syringe by the plunger.; The pre-filled syringe may contain small air bubbles; this is normal. Do not expel the air bubbles prior to administration.
2. |  | Do not remove the needle cover until ready to inject. Hold the syringe body and remove the needle cover by pulling straight off. Do not hold the plunger or plunger head while removing the needle cover. You may see a drop of liquid at the end of the needle. This is normal.
3. |  | Gently pinch the skin and administer subcutaneously at approximately 45° angle into the recommended injection site (i.e., upper arm, thigh, or abdomen).
4. |  | Inject all of the medication by pushing in the plunger all the way until the plunger head is completely between the needle guard activation clips. This is necessary to activate the needle guard.
5. |  | After injection, maintain pressure on the plunger head and remove the needle from the skin. Release pressure on the plunger head to allow the needle guard to cover the needle. Do not re-cap the pre-filled syringe.
6. | Discard the used syringe into a sharps container.

Administration Instructions for Single-Dose Pre-filled Pen

These administration instructions are intended for healthcare providers use only. Patients and caregivers should refer to the TEZSPIRE pre-filled pen ‘Instructions for Use’ for more detailed instructions on the preparation and administration of TEZSPIRE pre-filled pen [See Instructions for Use].

Patients/caregivers may inject after proper training in subcutaneous injection technique according to the ‘Instructions for Use’, and after the healthcare provider determines it is appropriate.

Refer to Figure 2 to identify the pre-filled pen components for use in the administration steps.

Do not remove the cap until you are ready to inject TEZSPIRE.

Figure 2 TEZSPIRE Pre-filled Pen Components

1. | Grab the middle of the pre-filled pen body to remove the pre-filled pen from its carton.; The pre-filled pen may contain small air bubbles; this is normal. Do not expel the air bubbles prior to administration.
2. |  | Do not remove the cap until ready to inject. Hold the pre-filled pen body with 1 hand and carefully pull the cap straight off with your other hand. Do not touch the needle or push the orange needle guard with your finger. Do not put the cap back on the pre-filled pen. You could cause the injection to happen too soon or damage the needle.
3. | Gently pinch the skin at the injection site or give the injection without pinching the skin.; Inject TEZSPIRE by following the steps into the recommended injection site (i.e., upper arm, thigh, or abdomen).; When injecting, you will hear the first click that tells you the injection has started. Press and hold the pre-filled pen for 15 seconds until you hear the second click. Do not change the position of the pre-filled pen after the injection has started.
4. |  |  | Position the pre-filled pen. Place the orange needle guard flat against the skin (90‑degree angle). Make sure you can see the viewing window.
5. |  |  | Press down firmly until you cannot see the orange needle guard. You will hear the first ‘click’, this tells you the injection has started. The orange plunger will move down in the viewing window during the injection.
6. |  |  | Hold down firmly for about 15 seconds. You will hear a second ‘click’, this tells you the injection has finished. The orange plunger will fill the viewing window.
7. |  |  | After you have completed the injection, lift the pre-filled pen straight up. The orange needle guard will slide down and lock into place over the needle.
8. | Discard the used pre-filled pen into a sharps container.

3 DOSAGE FORMS AND STRENGTHS

Injection: a clear to opalescent, colorless to light yellow solution available as:

- 210 mg/1.91 mL (110 mg/mL) solution in a single-dose glass vial.
- 210 mg/1.91 mL (110 mg/mL) solution in a single-dose pre-filled syringe.
- 210 mg/1.91 mL (110 mg/mL) solution in a single‑dose pre‑filled pen.

4 CONTRAINDICATIONS

TEZSPIRE is contraindicated in patients who have known hypersensitivity to tezepelumab-ekko or any of its excipients [see Warnings and Precautions (5.1)].

5 WARNINGS AND PRECAUTIONS

5.1 Hypersensitivity Reactions

Hypersensitivity reactions were observed in the clinical trials (e.g., rash and allergic conjunctivitis) following the administration of TEZSPIRE. Postmarketing cases of anaphylaxis have also been reported [see Contraindications (4) and Adverse Reactions (6.2)]. These reactions can occur within hours of administration, but in some instances have a delayed onset (i.e., days). In the event of a hypersensitivity reaction, consider the benefits and risks for the individual patient to determine whether to continue or discontinue treatment with TEZSPIRE.

5.2 Acute Asthma Symptoms or Deteriorating Disease

TEZSPIRE should not be used to treat acute asthma symptoms or acute exacerbations. Do not use TEZSPIRE to treat acute bronchospasm or status asthmaticus. Patients should seek medical advice if their asthma remains uncontrolled or worsens after initiation of treatment with TEZSPIRE.

5.3 Risk Associated with Abrupt Reduction of Corticosteroid Dosage

Do not discontinue systemic or inhaled corticosteroids abruptly upon initiation of therapy with TEZSPIRE. Reductions in corticosteroid dose, if appropriate, should be gradual and performed under the direct supervision of a physician. Reduction in corticosteroid dose may be associated with systemic withdrawal symptoms and/or unmask conditions previously suppressed by systemic corticosteroid therapy.

5.4 Parasitic (Helminth) Infection

Thymic stromal lymphopoietin (TSLP) may be involved in the immunological response to some helminth infections. Patients with known helminth infections were excluded from participation in clinical trials. It is unknown if TEZSPIRE will influence a patient’s response against helminth infections.

Treat patients with pre-existing helminth infections before initiating therapy with TEZSPIRE. If patients become infected while receiving treatment with TEZSPIRE and do not respond to anti-helminth treatment, discontinue treatment with TEZSPIRE until infection resolves.

5.5 Live Attenuated Vaccines

The concomitant use of TEZSPIRE and live attenuated vaccines has not been evaluated. The use of live attenuated vaccines should be avoided in patients receiving TEZSPIRE.

6 ADVERSE REACTIONS

The following clinically significant adverse reactions are described elsewhere in the labeling:

- Hypersensitivity Reactions [see Warnings and Precautions (5.1)]

6.1 Clinical Trials Experience

Because clinical trials are conducted under widely varying conditions, adverse reaction rates observed in the clinical trials of a drug cannot be directly compared to rates in the clinical trials of another drug and may not reflect the rates observed in practice.

Adverse Reactions in Adult and Pediatric Patients 12 Years of Age and Older with Asthma

The safety of TEZSPIRE in asthma was based on the pooled safety population from PATHWAY and NAVIGATOR, which consists of 665 adult and pediatric patients 12 years of age and older with severe asthma who received at least one dose of TEZSPIRE 210 mg subcutaneously once every 4 weeks. The two placebo-controlled clinical trials were of 52 weeks duration. In addition, a similar safety profile was seen in a trial that enrolled 150 adult patients with severe asthma who required treatment with daily oral corticosteroids [see Clinical Studies (14.1)].

Adverse reactions that occurred at an incidence greater than or equal to 3% and more common than in the placebo group from the pooled safety population (PATHWAY and NAVIGATOR) are shown in Table 1.

Table 1 Adverse Reactions with TEZSPIRE with Incidence Greater than or Equal to 3% and More Common than Placebo in Patients with Severe Asthma in the Pooled Safety Population (PATHWAY and NAVIGATOR)
Adverse Reaction | TEZSPIRE; N=665; % | Placebo; N=669; %
Pharyngitis [Pharyngitis (including Pharyngitis, Pharyngitis bacterial, Pharyngitis streptococcal and Viral pharyngitis)] | 4 | 3
Arthralgia | 4 | 3
Back pain | 4 | 3

Specific Adverse Reactions

Cardiovascular Events

In a randomized, double-blind, long term extension trial, patients 12 years and older with severe asthma from trials NAVIGATOR and the additional trial [see Clinical Studies (14.1)] received TEZSPIRE 210 mg subcutaneously every 4 weeks or placebo for up to 104 weeks. In the trial, the incidence rates (IR) per 100 patient-years (PY) for serious cardiac adverse events in patients treated with TEZSPIRE or placebo were 1.08 and 0.21, respectively, with an incidence rate difference (IRD) of 0.88 (95% CI: 0.24, 1.53). The types of serious cardiac adverse events were heterogeneous. In the trial, the IR per 100 PY for adjudicated major adverse cardiovascular events (MACE, defined as cardiovascular deaths, non-fatal myocardial infarctions, and non-fatal strokes) in patients treated with TEZSPIRE or placebo were 0.60 and 0.42, respectively, with an IRD of 0.18 (95% CI: -0.51, 0.75).

Injection Site Reactions

In the pooled safety population (PATHWAY and NAVIGATOR), in which TEZSPIRE or placebo was administered using the vial by a healthcare provider, injection site reactions (e.g., injection site erythema, injection site swelling, injection site pain) occurred at a rate of 3.3% in patients treated with TEZSPIRE compared with 2.7% in patients treated with placebo.

In an open-label trial of 216 patients with asthma in which TEZSPIRE was administered by healthcare providers and patients or caregivers using either the pre-filled pen or pre-filled syringe, injection site reactions (e.g., injection site erythema, injection site swelling, injection site pain) were observed in 5.7% patients using the pre-filled pen and 0% using the pre-filled syringe. However, the trial was not designed to compare injection site reactions between patients who received TEZSPIRE by the pre-filled pen versus pre-filled syringe.

Adverse Reactions in Adult Patients with Chronic Rhinosinusitis with Nasal Polyps

The safety of TEZSPIRE in CRSwNP was based on WAYPOINT, a randomized, double-blind, parallel group, multicenter, placebo-controlled trial of 52 weeks duration, which consisted of 203 adult patients aged 18 years and older on standard of care treatment for CRSwNP who received at least one dose of TEZSPIRE 210 mg subcutaneously once every 4 weeks [see Clinical Studies (14.2)].

Adverse reactions that occurred at an incidence greater than or equal to 3% and more common than in the placebo group from the safety population (WAYPOINT) are shown in Table 2.

Table 2 Adverse Reactions with TEZSPIRE with Incidence Greater than or Equal to 3% and More Common than Placebo in Patients with CRSwNP (WAYPOINT)
Adverse Reaction | TEZSPIRE; N=203; % | Placebo N=205; %
Nasopharyngitis | 18 | 10
Upper respiratory tract infection [Upper respiratory tract infection (including Upper respiratory tract infection and Viral upper respiratory tract infection)] | 12 | 8
Epistaxis | 6 | 3
Pharyngitis [Pharyngitis (including Pharyngitis, Pharyngitis bacterial, Pharyngitis streptococcal and Viral pharyngitis)] | 5 | 1
Back pain | 5 | 2
Influenza | 4 | 1
Injection site reaction [Injection site reaction (e.g., Injection site erythema, Injection site swelling and Injection site pain)] | 4 | 2
Arthralgia | 3 | 2

6.2 Postmarketing Experience

The following adverse reactions have been identified during post-approval use of TEZSPIRE. Because these reactions are reported voluntarily from a population of uncertain size, it is not always possible to reliably estimate their frequency or establish a causal relationship to drug exposure.

Hypersensitivity reactions: anaphylaxis

7 DRUG INTERACTIONS

No formal drug interaction studies have been performed with TEZSPIRE.

8 USE IN SPECIFIC POPULATIONS

8.1 Pregnancy

Risk Summary

There are no available data on TEZSPIRE use in pregnant women to evaluate for any drug-associated risk of major birth defects, miscarriage, or other adverse maternal or fetal outcomes. Placental transfer of monoclonal antibodies such as tezepelumab-ekko is greater during the third trimester of pregnancy; therefore, potential effects on a fetus are likely to be greater during the third trimester of pregnancy. In an enhanced pre- and post-natal development (ePPND) study conducted in cynomolgus monkeys, placental transport of tezepelumab-ekko was observed but there was no evidence of fetal harm following intravenous administration of tezepelumab-ekko throughout pregnancy at doses that produced maternal exposures up to 168 times the exposure at the maximum recommended human dose (MRHD) of 210 mg administered subcutaneously (see Data).

The estimated background risk of major birth defects and miscarriages for the indicated population is unknown. All pregnancies have a background risk of birth defect, loss, or other adverse outcomes. In the U.S. general population, the estimated background risk of major birth defects and miscarriage in clinically recognized pregnancies is 2% to 4% and 15% to 20%, respectively.

Clinical Considerations

Disease-associated maternal and/or embryo/fetal risk:

In women with poorly or moderately controlled asthma, evidence demonstrates that there is an increased risk of preeclampsia in the mother and prematurity, low birth weight, and small for gestational age in the neonate. The level of asthma control should be closely monitored in pregnant women and treatment adjusted as necessary to maintain optimal control.

Data

Animal Data

In the ePPND study, pregnant cynomolgus monkeys received tezepelumab-ekko from GD20 to GD22 (dependent on pregnancy determination), at the beginning of organogenesis, and once every 7 days until the end of gestation at doses that produced exposures up to 168 times that achieved with the MRHD (on an AUC basis with maternal intravenous doses up to 300 mg/kg/week). There were no tezepelumab-ekko related adverse effects on maternal health, pregnancy outcome, embryo-fetal development, or neonatal growth and development up to 6.5 months of age. Tezepelumab-ekko crossed the placenta in cynomolgus monkeys and tezepelumab-ekko serum concentrations were 0.5- to 6.7-fold higher in infants relative to maternal animals.

8.2 Lactation

Risk Summary

There is no information regarding the presence of tezepelumab-ekko in human milk, its effects on the breastfed infant, or its effects on milk production. However, tezepelumab-ekko is a human monoclonal antibody immunoglobulin G2λ (IgG2λ), and immunoglobulin G (IgG) is present in human milk in small amounts. Tezepelumab‑ekko was present in the milk of cynomolgus monkeys postpartum following dosing during pregnancy (see Data). The developmental and health benefits of breastfeeding should be considered along with the mother's clinical need for TEZSPIRE and any potential adverse effects on the breastfed infant from TEZSPIRE or from the underlying maternal condition.

Data

Animal Data

In a prenatal and postnatal development study in cynomolgus monkeys, tezepelumab-ekko concentrations in milk were up to 0.5% of the maternal serum concentrations after intravenous administration of tezepelumab-ekko up to 300 mg/kg/week (168 times the exposures based on AUC achieved at MRHD). The concentration of tezepelumab-ekko in animal milk does not necessarily predict the concentration of drug in human milk.

8.4 Pediatric Use

Asthma

The safety and effectiveness of TEZSPIRE for the add-on maintenance treatment of severe asthma have been established in pediatric patients aged 12 years and older [see Adverse Reactions (6.1) and Clinical Studies (14.1)]. Use of TEZSPIRE for this indication is supported by evidence from a total of 82 pediatric patients aged 12 to 17 years enrolled in NAVIGATOR and received treatment with TEZSPIRE 210 mg subcutaneously every 4 weeks (n=41) or placebo (n=41). Compared with placebo, improvements in annualized asthma exacerbation (rate ratio 0.70; 95% CI 0.34, 1.46) and FEV1 (LS mean change versus placebo 0.17 L; 95% CI -0.01, 0.35) were observed in pediatric patients treated with TEZSPIRE. The safety profile and pharmacodynamic responses in pediatric patients were generally similar to the overall study population.

The safety and effectiveness of TEZSPIRE have not been established in patients younger than 12 years of age with asthma.

CRSwNP

The safety and effectiveness of TEZSPIRE for the add-on maintenance treatment of inadequately controlled CRSwNP have been established in pediatric patients aged 12 years and older. Use of TEZSPIRE for this indication is supported by evidence from the adequate and well-controlled study of TEZSPIRE in adults (WAYPOINT) [see Clinical Studies (14.2)] with the following additional data:

- Pharmacokinetic (PK) data from adult and pediatric patients aged 12 years and older with severe asthma and adult patients with CRSwNP [see Clinical Pharmacology (12.3)].
- Safety data in pediatric patients aged 12 years and older with severe asthma [see Adverse Reactions (6.1)].

The safety and effectiveness of TEZSPIRE have not been established in patients younger than 12 years of age with CRSwNP.

8.5 Geriatric Use

Asthma

Of the 665 patients with asthma treated with TEZSPIRE in clinical trials (PATHWAY and NAVIGATOR) for severe asthma, 119 patients (18%) were 65 years or older. No overall differences in safety or effectiveness of TEZSPIRE have been observed between patients 65 years of age and older and younger patients [see Adverse Reactions (6.1) and Clinical Studies (14.1)].

CRSwNP

Of the 203 patients with CRSwNP treated with TEZSPIRE in a clinical trial (WAYPOINT) for CRSwNP, 29 patients (14%) were 65 years or older. No overall differences in safety or effectiveness of TEZSPIRE have been observed between patients 65 years of age and older and younger adult patients [see Adverse Reactions (6.1) and Clinical Studies (14.2)].

11 DESCRIPTION

Tezepelumab-ekko, a thymic stromal lymphopoietin (TSLP) blocker, is a human monoclonal antibody immunoglobulin G2λ (IgG2λ) produced in Chinese hamster ovary (CHO) cells by recombinant DNA technology. Tezepelumab-ekko has a molecular weight of approximately 147 kDa.

TEZSPIRE (tezepelumab-ekko) injection is a sterile, preservative-free, clear to opalescent, colorless to light yellow solution for subcutaneous injection supplied in a single-dose vial, single-dose pre-filled syringe or single‑dose pre‑filled pen.

Each single-dose vial, pre-filled syringe or pre‑filled pen delivers 1.91 mL containing 210 mg tezepelumab-ekko, glacial acetic acid (2.8 mg), L-proline (48 mg), polysorbate 80 (0.19 mg), sodium hydroxide, and water for injection. The pH is 5.2.

12 CLINICAL PHARMACOLOGY

12.1 Mechanism of Action

Tezepelumab-ekko is a thymic stromal lymphopoietin (TSLP) blocker, human monoclonal antibody IgG2λ that binds to human TSLP with a dissociation constant of 15.8 pM and blocks its interaction with the heterodimeric TSLP receptor. TSLP is a cytokine mainly derived from epithelial cells and occupies an upstream position in inflammatory cascades.

Airway and mucosal inflammation are important components of the pathogenesis of asthma and CRSwNP. Multiple cell types (e.g., mast cells, eosinophils, neutrophils, macrophages, lymphocytes, ILC2 cells) and mediators (e.g., histamine, eicosanoids, leukotrienes, cytokines) are involved in airway and mucosal inflammation. Increased levels of TSLP mRNA and protein are found in the airways of patients with asthma as well as in nasal polyp tissue. Blocking TSLP with tezepelumab-ekko reduces biomarkers and cytokines associated with inflammation including blood eosinophils, airway submucosal eosinophils, IgE, FeNO, IL-5, and IL-13; however, the mechanism of tezepelumab-ekko action in asthma and CRSwNP has not been definitively established.

12.2 Pharmacodynamics

In NAVIGATOR, administration of TEZSPIRE 210 mg subcutaneously every 4 weeks (n=528) reduced blood eosinophils counts, FeNO, IL-5 concentration and IL-13 concentration from baseline compared with placebo (n=531) with an onset of effect 2 weeks after initiation of treatment and sustained reduction on treatment to 52 weeks. TEZSPIRE caused a slow but progressive reduction in serum total IgE concentration throughout 52 weeks of treatment. Similar effects were seen in PATHWAY.

In WAYPOINT, administration of TEZSPIRE 210 mg subcutaneously every 4 weeks (n=203) resulted in reductions from baseline of blood eosinophils, FeNO (in participants with co-morbid asthma [about 60% of patients]) and serum IgE as compared to placebo (n=205). Blood eosinophils were reduced beginning at Week 4, the first observed timepoint, with reductions maintained through Week 52. Reductions in FeNO and serum IgE were observed during the treatment period at Weeks 24 and 52.

12.3 Pharmacokinetics

The pharmacokinetics of tezepelumab-ekko is similar in patients with asthma and CRSwNP.

The pharmacokinetics of tezepelumab-ekko were dose-proportional following administration of a single subcutaneous dose over a dose range from 0.01 to 2 times the recommended dose. With an every 4 weeks dosing regimen, tezepelumab-ekko achieves steady-state after 12 weeks and the accumulation ratio for Ctrough is 1.86-fold.

Absorption

Following subcutaneous administration, the maximum serum concentration was reached in approximately 3 to 10 days. Based on population pharmacokinetic analysis, the estimated absolute bioavailability was approximately 77%. There was no clinically relevant difference in bioavailability when administered to different injection sites (abdomen, thigh, or upper arm).

Distribution

Based on population pharmacokinetic analysis, central and peripheral volume of distribution of tezepelumab-ekko were 3.9 L and 2.2 L, respectively, for a 70 kg individual.

Elimination

As a human monoclonal antibody, tezepelumab-ekko is eliminated by intracellular catabolism and there is no evidence of target-mediated clearance within the studied dose range. Based on population pharmacokinetic analysis, the estimated clearance for tezepelumab-ekko was 0.17 L/d for a 70 kg individual. The elimination half-life was approximately 26 days.

Metabolism

Tezepelumab-ekko is a human monoclonal antibody (IgG2λ) that is degraded by proteolytic enzymes widely distributed in the body and not metabolized by hepatic enzymes.

Specific Populations

Age, Sex, Race

Based on population pharmacokinetic analysis, age (12 to 80 years), sex and race (White, Black, Asian, Other) had no clinically meaningful effects on the pharmacokinetics of tezepelumab-ekko.

Body Weight

Based on population pharmacokinetic analysis, higher body weight was associated with lower exposure. However, the effect of body weight on exposure had no meaningful impact on efficacy or safety and does not require dose adjustment.

Pediatric Patients

CRSwNP

Clinical studies have not been conducted in pediatric patients aged 12 years and older with CRSwNP. Tezepelumab-ekko exposures are expected to be comparable between adults and pediatric patients aged 12 years and older at the recommended subcutaneous dosage (210 mg every 4 weeks) for CRSwNP.

Patients with Renal impairment

No formal clinical studies have been conducted to investigate the effect of renal impairment on tezepelumab-ekko. The population pharmacokinetic analysis included 320 (23%) subjects with mild renal impairment and 38 (3%) subjects with moderate renal impairment. Tezepelumab-ekko clearance was similar in patients with mild renal impairment (estimated creatinine clearance 60 to 89 mL/min), moderate renal impairment (estimated creatinine clearance 30 to 59 mL/min) and those with normal renal function (estimated creatinine clearance ≥ 90 mL/min). Tezepelumab-ekko has not been studied in patients with severe renal impairment (estimated creatinine clearance < 30 mL/min).

Patients with Hepatic impairment

No formal clinical studies have been conducted to investigate the effect of hepatic impairment on tezepelumab-ekko. Since tezepelumab-ekko is degraded by proteolytic enzymes widely distributed in the body and not metabolized by hepatic-specific enzymes, change in hepatic function is not expected to influence tezepelumab-ekko clearance.

Drug Interaction Studies

No formal drug interaction studies have been conducted with tezepelumab-ekko. Based on the population pharmacokinetic analysis, commonly co-administered asthma medications (leukotriene receptor antagonist, theophylline/aminophylline, oral and inhaled corticosteroid) had no clinically meaningful effect on tezepelumab-ekko clearance.

12.6 Immunogenicity

The observed incidence of anti-drug antibodies is highly dependent on the sensitivity and specificity of the assay. Differences in assay methods preclude meaningful comparisons of the incidence of anti-drug antibodies in the studies described below with the incidence of anti-drug antibodies in other studies, including those of tezepelumab-ekko or of other tezepelumab products.

In patients with asthma (NAVIGATOR and an additional trial), anti-drug antibodies (ADA) were detected at any time in 29 (5%) out of 601 patients who received TEZSPIRE at the recommended dosing regimen during the 48 to 52‑week study period. Of these 29 patients, 11 patients (2% of patients treated with TEZSPIRE) developed treatment-emergent antibodies and 1 patient (<1% of patients treated with TEZSPIRE) developed neutralizing antibodies. ADA titers were generally low and often transient. No evidence of ADA impact on pharmacokinetics, pharmacodynamics, efficacy, or safety was observed.

In patients with CRSwNP (WAYPOINT), a treatment-emergent ADA response developed in 5 (3%) out of 164 patients treated with TEZSPIRE at the recommended dosage regimen during the 52-week treatment period. Neutralizing antibodies were detected in 1 of the ADA positive patients. While there was no observed impact of ADA on pharmacokinetics, pharmacodynamics, efficacy, or safety, there were insufficient numbers of patients with treatment‑emergent ADA to make a formal assessment in CRSwNP.

13 NONCLINICAL TOXICOLOGY

13.1 Carcinogenesis, Mutagenesis, Impairment of Fertility

Animal studies have not been conducted to evaluate the carcinogenic potential of tezepelumab-ekko. The malignancy risk in humans from an antibody that blocks TSLP ligand, such as tezepelumab-ekko, is currently unknown.

Male and female fertility was unaffected based upon no observed adverse histopathological findings in the reproductive organs and no changes in menstrual cycle or semen analysis in sexually mature cynomolgus monkeys that received tezepelumab-ekko for 26 weeks at subcutaneous doses up to 300 mg/kg/week (approximately 134 times the MRHD on an AUC basis).

14 CLINICAL STUDIES

14.1 Clinical Studies in Patients with Asthma

The efficacy of TEZSPIRE for add-on maintenance treatment of severe asthma was evaluated in two randomized, double-blind, parallel group, placebo-controlled clinical trials (PATHWAY [NCT02054130] and NAVIGATOR [NCT03347279]) of 52 weeks duration. The two trials enrolled a total of 1,609 patients 12 years of age and older with severe asthma.

PATHWAY was a 52-week dose-ranging exacerbation trial that enrolled 550 adult patients with severe asthma who received treatment with tezepelumab-ekko 70 mg subcutaneously every 4 weeks, TEZSPIRE 210 mg subcutaneously every 4 weeks, tezepelumab-ekko 280 mg subcutaneously every 2 weeks, or placebo subcutaneously. Patients were required to have a history of 2 or more asthma exacerbations requiring oral or injectable corticosteroid treatment or 1 asthma exacerbation resulting in hospitalization in the past 12 months.

NAVIGATOR was a 52-week exacerbation trial that enrolled 1,061 patients (adult and pediatric patients 12 years of age and older) with severe asthma who received treatment with TEZSPIRE 210 mg subcutaneously every 4 weeks or placebo subcutaneously every 4 weeks. Patients were required to have a history of 2 or more asthma exacerbations requiring oral or injectable corticosteroid treatment or resulting in hospitalization in the past 12 months.

In both PATHWAY and NAVIGATOR, patients were required to have an Asthma Control Questionnaire 6 (ACQ-6) score of 1.5 or more at screening and reduced lung function at baseline [pre-bronchodilator forced expiratory volume in 1 second (FEV1) below 80% predicted in adults, and below 90% predicted in adolescents]. Patients were required to have been on regular treatment with medium or high-dose inhaled corticosteroids (ICS) and at least one additional asthma controller, with or without oral corticosteroids (OCS). Patients continued background asthma therapy throughout the duration of the trials. In both trials, patients were enrolled without requiring a minimum baseline level of blood eosinophils or FeNO.

The demographics and baseline characteristics of PATHWAY and NAVIGATOR are provided in Table 3 below.

Table 3 Demographics and Baseline Characteristics of Patients in PATHWAY and NAVIGATOR

 | PATHWAY N=550 | NAVIGATOR N=1,059
Mean age (year) (SD) | 52 (12) | 50 (16)
Female (%) | 66 | 64
White (%) | 92 | 62
Black or African American (%) | 3 | 6
Asian (%) | 3 | 28
Hispanic or Latino (%) | 1 | 15
Never smoked (%) | 81 | 80
High-dose ICS use (%) | 49 | 75
OCS use (%) | 9 | 9
Mean number of exacerbations in previous year (SD) | 2.4 (1.2) | 2.8 (1.4)
Mean duration of asthma (years) (SD) | 17 (12) | 22 (16)
Mean baseline % predicted FEV1 (SD) | 60 (13) | 63 (18)
Mean post-bronchodilator FEV1 reversibility (%) (SD) | 23 (20) | 15 (15)
Mean baseline blood EOS count (cells/µL) (SD) | 371 (353) | 340 (403)
Positive serum specific IgE to any perennial allergen (%) [In the FEIA panel] | 46 | 64
Mean FeNO (ppb) (SD) | 35 (39) | 44 (41)

EOS, Eosinophils; FEIA, Fluorescent enzyme immunoassay; FeNO, Fractional exhaled nitric oxide; FEV1, Forced expiratory volume in one second; ICS, Inhaled corticosteroid, IgE, Immunoglobulin E; OCS, Oral corticosteroid; ppb, Parts per billion; SD, Standard deviation

The results summarized below are for the recommended TEZSPIRE 210 mg subcutaneously every 4 weeks dosing regimen.

Exacerbations

The primary endpoint for PATHWAY and NAVIGATOR was the rate of clinically significant asthma exacerbations measured over 52 weeks. Clinically significant asthma exacerbations were defined as worsening of asthma requiring the use of or increase in oral or injectable corticosteroids for at least 3 days, or a single depo-injection of corticosteroids, and/or emergency department visits requiring use of oral or injectable corticosteroids and/or hospitalization.

In both PATHWAY and NAVIGATOR, patients receiving TEZSPIRE had significant reductions in the annualized rate of asthma exacerbations compared to placebo. There were also fewer exacerbations requiring emergency room visits and/or hospitalization in patients treated with TEZSPIRE compared with placebo (Table 4).

Table 4 Rate of Clinically Significant Exacerbations Over 52 Weeks in PATHWAY and NAVIGATOR

Trial | Treatment | Exacerbations per year
Trial | Treatment | Rate | Rate Ratio (95% CI)
Annualized Asthma Exacerbation Rate
PATHWAY | TEZSPIRE (N=137) | 0.20 | 0.29 (0.16, 0.51)
PATHWAY | Placebo (N=138) | 0.72 | 0.29 (0.16, 0.51)
NAVIGATOR | TEZSPIRE (N=528) | 0.93 | 0.44 (0.37, 0.53)
NAVIGATOR | Placebo (N=531) | 2.10 | 0.44 (0.37, 0.53)
Exacerbations requiring emergency room visit/hospitalization
PATHWAY | TEZSPIRE (N=137) | 0.03 | 0.15 (0.04, 0.58)
PATHWAY | Placebo (N=138) | 0.18 | 0.15 (0.04, 0.58)
NAVIGATOR | TEZSPIRE (N=528) | 0.06 | 0.21 (0.12, 0.37)
NAVIGATOR | Placebo (N=531) | 0.28 | 0.21 (0.12, 0.37)
Exacerbations requiring hospitalization
PATHWAY | TEZSPIRE (N=137) | 0.02 | 0.14 (0.03, 0.71)
PATHWAY | Placebo (N=138) | 0.14 | 0.14 (0.03, 0.71)
NAVIGATOR | TEZSPIRE (N=528) | 0.03 | 0.15 (0.07, 0.22)
NAVIGATOR | Placebo (N=531) | 0.19 | 0.15 (0.07, 0.22)

In NAVIGATOR, patients receiving TEZSPIRE experienced fewer exacerbations than those receiving placebo regardless of baseline levels of blood eosinophils or FeNO (Figure 3). Similar results were seen in PATHWAY.

Figure 3 Annualized Asthma Exacerbation Rate Ratio Over 52 Weeks Across Different Baseline Biomarkers in NAVIGATOR

The time to first exacerbation was longer for the patients receiving TEZSPIRE compared with placebo in NAVIGATOR (Figure 4). Similar findings were seen in PATHWAY.

Figure 4 Kaplan-Meier Cumulative Incidence Curves for Time to First Exacerbation in NAVIGATOR

Lung Function

Change from baseline in FEV1 was assessed as a secondary endpoint in PATHWAY and NAVIGATOR. Compared with placebo, TEZSPIRE provided clinically meaningful improvements in the mean change from baseline in FEV1 in both trials (Table 5).

Table 5 Mean Change from Baseline in Pre-Bronchodilator FEV1 at End of Trial in PATHWAY and NAVIGATOR [Week 52 in PATHWAY, Week 52 in NAVIGATOR]
Trial | Treatment | LS Mean Change from Baseline (L) | Difference from Placebo; (95% CI)
PATHWAY | TEZSPIRE (N=133) [Number of patients contributing to the full analysis (FA) with at least 1 change from baseline value] | 0.08 | 0.13 (0.03, 0.23)
PATHWAY | Placebo (N=138) | -0.06 | 0.13 (0.03, 0.23)
NAVIGATOR | TEZSPIRE (N=527) | 0.23 | 0.13 (0.08, 0.18)
NAVIGATOR | Placebo (N=531) | 0.10 | 0.13 (0.08, 0.18)

In NAVIGATOR, improvement in FEV1 was seen as early as 2 weeks after initiation of treatment and was sustained through week 52 (Figure 5).

Figure 5 Mean Change (95% CI) from Baseline in Pre-Bronchodilator FEV1 (L) in NAVIGATOR

Patient Reported Outcomes

Changes from baseline in Asthma Control Questionnaire 6 (ACQ-6) and Standardized Asthma Quality of Life Questionnaire for ages 12 and older [AQLQ(S)+12] were also assessed as secondary endpoints in PATHWAY and NAVIGATOR. In both trials, more patients treated with TEZSPIRE compared to placebo had a clinically meaningful improvement in ACQ-6 and AQLQ(S)+12. Clinically meaningful improvement (responder rate) for both measures was defined as improvement in score of 0.5 or more at end of trial. In NAVIGATOR, the ACQ-6 responder rate for TEZSPIRE was 86% compared with 77% for placebo (OR=1.99; 95% CI 1.43, 2.76) and the AQLQ(S)+12 responder rate for TEZSPIRE was 78% compared with 72% for placebo (OR=1.36; 95% CI 1.02, 1.82). Similar findings were seen in PATHWAY.

Additional Trial

In a randomized, double-blind, parallel group, placebo-controlled clinical trial, the effect of TEZSPIRE (210 mg subcutaneously every 4 weeks) on reducing the use of maintenance OCS was evaluated. The trial enrolled 150 adult patients with severe asthma who required treatment with daily OCS (7.5 mg to 30 mg per day) in addition to regular use of high-dose ICS and a long-acting beta-agonist with or without additional controller(s). The primary endpoint was categorized percent reduction from baseline of the final OCS dose at Week 48 (≥90% reduction, ≥75% to <90% reduction, ≥50% to <75% reduction, >0% to <50% reduction, and no change or any increase in OCS), while maintaining asthma control. TEZSPIRE did not demonstrate a statistically significant reduction in maintenance OCS dose compared with placebo (cumulative OR=1.28; 95% CI 0.69, 2.35).

14.2 Clinical Studies in Patients with Chronic Rhinosinusitis with Nasal Polyps

The efficacy of TEZSPIRE for add-on maintenance treatment of inadequately controlled chronic rhinosinusitis with nasal polyps (CRSwNP) was evaluated in a randomized, double-blind, parallel group, multicenter, placebo-controlled trial (WAYPOINT [NCT04851964]) of 52 weeks treatment duration conducted in 408 patients aged 18 years and older on standard of care treatment for CRSwNP. This study included patients with symptomatic CRSwNP despite treatment with nasal corticosteroids, and who had systemic corticosteroids within the past 12 months and/or any history of sino-nasal surgery, or with contraindications and/or intolerance to either.

Patients received TEZSPIRE 210 mg or placebo subcutaneously every 4 weeks for 52 weeks in addition to nasal corticosteroid treatment for CRSwNP.

The demographics and baseline characteristics of patients enrolled in WAYPOINT are provided in Table 6.

Table 6 Demographics and Baseline Characteristics of Adult Patients in WAYPOINT
 | WAYPOINT; N=408 [Number of patients (N) =407 for mean total NPS; N=406 for mean bi-weekly NCS and mean bi-weekly loss of smell; N=404 for mean LMK sinus CT total score and mean blood eosinophils; N=389 for mean total IgE.]
Mean age (years) (SD) | 50 (14)
Male (%) | 65
Mean CRSwNP duration (years) (SD) | 13 (10)
Patients with ≥1 prior surgery (%) | 71
Patients with systemic corticosteroid use for CRSwNP in the previous year (%) | 58
Mean total NPS [Higher scores indicate greater disease severity or symptom severity.] (SD), range 0-8 | 6.1 (1.2)
Mean bi-weekly NCS (SD), range 0-3 | 2.6 (0.5)
Mean LMK sinus CT total score (SD), range 0-24 | 19 (4)
Mean bi-weekly loss of smell (SD), range 0-3 | 2.9 (0.4)
Mean blood eosinophils (cells/µL) (SD) | 358 (238)
Mean total IgE IU/mL (SD) | 176 (285)
Asthma [Includes patients with asthma or AERD or NSAID-ERD. All but 3 patients with AERD or NSAID-ERD included in this subgroup also had a diagnosis of asthma reported.] (%) | 61
NSAID-ERD/AERD (%) | 17

AERD, Aspirin exacerbated respiratory disease; CRSwNP, Chronic rhinosinusitis with nasal polyps; CT, Computed tomography; IgE, Immunoglobulin E; IU, International units; LMK, Lund-Mackay; NCS, Nasal congestion score; NPS, Nasal polyp score; NSAID‑ERD, Nonsteroidal anti-inflammatory drug exacerbated respiratory disease; SD, Standard deviation

The co-primary efficacy endpoints were change from baseline in total nasal polyp score (NPS) evaluated by nasal endoscopy at Week 52 as graded by independent blinded assessors, and change from baseline in bi-weekly mean nasal congestion score (NCS) evaluated at Week 52. For total NPS, polyps on each side of the nose were graded on a categorical scale (0=no polyps, 1=small polyps in the middle meatus not reaching below the inferior border of the middle turbinate, 2=polyps reaching below the lower border of the middle turbinate, 3=polyps reaching the lower border of the inferior turbinate or a middle meatal polyp with a score of 2 with any additional polyp medial to the middle turbinate, 4=large polyps causing complete or near complete obstruction of the inferior nasal cavity [i.e. touching the floor of the nose]) for a total score of 0 to 8. Nasal congestion was rated daily by the patients on a 0 to 3 categorical severity scale (0=none, 1=mild, 2=moderate, 3=severe).

Statistically significant efficacy was observed in WAYPOINT for the co-primary endpoints of improvement in total NPS and in bi-weekly mean NCS at Week 52 (Table 7).

Table 7 Results of Change from Baseline in Total Nasal Polyp Score and Bi-weekly Mean Nasal Congestion Score at Week 52 in Adults with CRSwNP (WAYPOINT)
 | TEZSPIRE; 210 mg Q4W; (N=203) |  | Placebo; (N=205) |  | LS mean difference vs. placebo; (95% CI)
Scores | Baseline mean | LS mean change | Baseline mean | LS mean change
NPS | 6.1 | -2.47 | 6.1 | -0.47 | -2.01; (-2.33, -1.68)
NCS | 2.59 | -1.76 | 2.55 | -0.81 | -0.95; (-1.12, -0.78)
LS mean change, Least squared mean change from baseline; reduction in score indicates improvement; NCS, Nasal congestion score; NPS, Nasal polyp score

Figure 6 demonstrates the time course of improvement in the mean change from baseline in NPS.

Figure 6 LS Mean Change from Baseline in Total Nasal Polyp Score up to Week 52 in Adults (WAYPOINT)

Figure 7 demonstrates the time course of improvement in the bi-weekly mean change from baseline in NCS.

Figure 7 LS Mean Change from Baseline in Bi-weekly Mean Nasal Congestion Score up to Week 52 in Adults (WAYPOINT)

Key secondary endpoints at Week 52 included time to surgery decision and/or systemic corticosteroid use for nasal polyps, change from baseline in loss of smell, and change from baseline in Lund-Mackay (LMK) sinus CT scan score.

TEZSPIRE significantly reduced the proportion of patients with need for sino-nasal surgery or systemic corticosteroids by 92% compared to placebo over 52 weeks (Hazard Ratio: 0.08; 95% CI: 0.03, 0.17) (Figure 8).

Figure 8 Kaplan Meier Curve for Time to First Systemic Corticosteroid Use and/or Sino-Nasal Surgery Decision Over 52 Weeks in Adults (WAYPOINT)

TEZSPIRE significantly reduced the proportion of patients requiring sino-nasal surgery by 98% compared to placebo over 52 weeks (Hazard Ratio: 0.02; 95% CI: 0.00, 0.09) and significantly reduced the proportion of patients requiring systemic corticosteroids for CRSwNP by 88% compared to placebo over 52 weeks (Hazard Ratio: 0.12; 95% CI: 0.04, 0.27).

The loss of smell score was based on a subject’s daily rating of the severity of their worst difficulty with sense of smell over the past 24 hours on a 0 to 3 scale (0=none, 1=mild, 2=moderate, 3=severe). The loss of smell score was calculated every 2 weeks as the bi-weekly mean. TEZSPIRE significantly improved the loss of smell compared to placebo. The LS mean difference for loss of smell at Week 52 in the TEZSPIRE group versus placebo was -1.01 [95% CI: -1.18, -0.83].

The LMK sinus CT scan score evaluated the opacification of each sinus at baseline and Week 52 using a 0 to 2 scale (0=no abnormality; 1=partial opacification, 2=total opacification) deriving a maximum score of 12 per side and a total maximum score of 24 (higher scores indicate more opacification). A significant decrease in the LMK sinus CT scan score was observed. The LS mean difference for LMK sinus CT scan score at Week 52 in the TEZSPIRE group versus placebo was -5.76 [95% CI: -6.45, -5.07].

16 HOW SUPPLIED/STORAGE AND HANDLING

How Supplied

TEZSPIRE (tezepelumab-ekko) injection is a sterile, preservative-free, clear to opalescent, colorless to light yellow solution supplied as a single-dose vial, single-dose pre-filled syringe with a fixed 27-gauge ½ inch needle with a needle cover or single-dose pre-filled pen with a fixed 27-gauge ½ inch needle with a needle cover. The vial, pre-filled syringe and pre-filled pen, including the needle cover and stopper, are not made with natural rubber latex.

TEZSPIRE is available as:

- Single-Dose Vial: Carton contains one 210 mg/1.91 mL (110 mg/mL) glass vial (NDC 55513‑100‑01)
- Single-Dose Pre-filled Syringe: Carton contains one 210 mg/1.91 mL (110 mg/mL) pre-filled syringe (NDC 55513‑112‑01)
- Single-Dose Pre-filled Pen: Carton contains one 210 mg/1.91 mL (110 mg/mL) pre-filled pen (NDC 55513-123‑01)

Storage and Handling

Store refrigerated between 36°F to 46°F (2°C to 8°C). If necessary, TEZSPIRE may be kept at room temperature between 68°F to 77˚F (20°C to 25°C) for a maximum of 30 days. Do not put back in the refrigerator once TEZSPIRE has reached room temperature. After removal from the refrigerator, TEZSPIRE must be used within 30 days or discarded.

Store TEZSPIRE in original carton to protect from light until time of use.

Do not freeze. Do not shake. Do not expose to heat.

17 PATIENT COUNSELING INFORMATION

Advise the patient and/or caregiver to read the FDA-approved patient labeling (Patient Information and Instructions for Use).

Hypersensitivity Reactions

Inform patients that hypersensitivity reactions (e.g., anaphylaxis, rash and allergic conjunctivitis) can occur following administration of TEZSPIRE [see Contraindications (4) and Adverse Reactions (6)]. These reactions can occur within hours of administration, but in some instances have a delayed onset (i.e., days). Instruct patients to contact their healthcare provider if they experience symptoms of an allergic reaction [see Warnings and Precautions (5.1)].

Not for Acute Symptoms or Deteriorating Disease

Inform patients that TEZSPIRE does not treat acute asthma symptoms or acute exacerbations. Inform patients to seek medical advice if their asthma remains uncontrolled or worsens after initiation of treatment with TEZSPIRE [see Warnings and Precautions (5.2)].

Risk Associated with Abrupt Reduction of Corticosteroid Dosage

Inform patients to not discontinue systemic or inhaled corticosteroids except under the direct supervision of a healthcare provider. Inform patients that reduction in corticosteroid dose may be associated with systemic withdrawal symptoms and/or unmask conditions previously suppressed by systemic corticosteroid therapy [see Warnings and Precautions (5.3)].

Administration of Vaccines

Instruct patients to inform the healthcare provider that they are taking TEZSPIRE prior to a potential vaccination [see Warnings and Precautions (5.5)].

Proper Storage and Disposal

Advise patients to refrigerate TEZSPIRE at 36°F to 46°F (2°C to 8°C). TEZSPIRE may be kept at room temperature between 68°F to 77˚F (20°C to 25°C) for a maximum of 30 days [see How Supplied/Storage and Handling (16)]. Inform patients and caregivers of the need for proper disposal of the pre-filled pen after use, including the use of a sharps disposal container.

Manufactured by: AstraZeneca AB, Södertälje, Sweden SE-15185

US License No. 2059

At: Amgen Inc., One Amgen Center Drive, Thousand Oaks, CA 91320-1799

Marketed by: Amgen Inc. and AstraZeneca AB

©AstraZeneca and Amgen 2025

TEZSPIRE is a trademark of Amgen Inc. and AstraZeneca.

PATIENT INFORMATION

TEZSPIRE® (TEZ-SPY-ER)

(tezepelumab-ekko)

injection, for subcutaneous use

What is TEZSPIRE?

TEZSPIRE is a prescription medicine used:

- with other asthma medicines for the maintenance treatment of severe asthma in people 12 years of age and older whose asthma is not controlled with their current asthma medicine.
- with other medicines for the maintenance treatment of chronic rhinosinusitis with nasal polyps (CRSwNP) in people 12 years of age and older whose CRSwNP is not controlled with their current CRSwNP medicine.

TEZSPIRE helps:

- prevent severe asthma attacks (exacerbations) and can improve your breathing.
- reduce the size of your polyps, improve symptoms i.e. nasal congestion and loss of smell, and reduce the need for oral corticosteroids and surgery for your nasal polyps.

TEZSPIRE is not used to treat sudden breathing problems. Tell your healthcare provider if your asthma does not get better or if it gets worse after you start treatment with TEZSPIRE.

It is not known if TEZSPIRE is safe and effective in children under 12 years of age for the treatment of asthma.

It is not known if TEZSPIRE is safe and effective in children under 12 years of age for the treatment of CRSwNP.

Do not use TEZSPIRE if you:

- are allergic to tezepelumab‑ekko or any of the ingredients in TEZSPIRE. See the end of this Patient Information leaflet for a complete list of ingredients in TEZSPIRE.

Before using TEZSPIRE, tell your healthcare provider about all of your medical conditions, including if you:

- have ever had a severe allergic reaction (hypersensitivity).
- have a parasitic (helminth) infection.
- have recently received or are scheduled to receive any live attenuated vaccinations. People who receive TEZSPIRE should not receive live attenuated vaccines.
- are pregnant, think you may be pregnant, or plan to become pregnant. It is not known if TEZSPIRE may harm your unborn baby.
- are breastfeeding or plan to breastfeed. It is not known if TEZSPIRE passes into your breast milk. Talk to your healthcare provider about the best way to feed your baby if you use TEZSPIRE.

Tell your healthcare provider about all the medicines you take, including prescription and over-the-counter medicines, vitamins, and herbal supplements.

Do not change or stop your other medicines, including corticosteroid medicines or other asthma medicines unless your healthcare provider tells you to. This may cause other symptoms that were controlled by those medicines to come back.

How should I use TEZSPIRE?

- See the detailed Instructions for Use that comes with TEZSPIRE pre-filled pen for information on how to prepare and inject TEZSPIRE.
- Use TEZSPIRE exactly as prescribed by your healthcare provider.
- TEZSPIRE is injected under your skin (subcutaneously) 1 time every 4 weeks.
- TEZSPIRE comes in a single-dose vial, in a single-dose pre-filled syringe, and in a single-dose pre-filled pen.
- Your healthcare provider can inject you with TEZSPIRE in a healthcare setting.
- If your healthcare provider decides that you or a caregiver can give the injections of TEZSPIRE, you or your caregiver should receive training on the right way to prepare and inject the TEZSPIRE single dose pre-filled pen.
- Do not try to inject TEZSPIRE until you or your caregiver have been shown the right way by your healthcare provider.
- If you miss a dose, inject a dose as soon as possible. After that, you can continue to use TEZSPIRE on your usual injection day. If you did not notice that you missed a dose until it is time for your next scheduled dose, skip the missed dose and inject the next scheduled dose as planned. Do not inject more than one dose in a day. If you have questions about when to inject TEZSPIRE, contact your healthcare provider.

What are the possible side effects of TEZSPIRE?

TEZSPIRE may cause serious side effects, including:

- allergic (hypersensitivity) reactions, including anaphylaxis. Serious allergic reactions can happen after you get your TEZSPIRE injection. Allergic reactions can sometimes happen hours or days after you get a dose of TEZSPIRE. Call your healthcare provider or get emergency medical care if you get any of the following symptoms of allergic reaction:

∘ rash
∘ hives
∘ swelling of your face, mouth, and tongue

∘ breathing problems
∘ red, itchy, swollen, or inflamed eyes
∘ fainting, dizziness, feeling lightheaded

The most common side effects of TEZSPIRE include:

- sore throat (pharyngitis)
- common cold symptoms (nasopharyngitis)
- flu

- joint pain (arthralgia)
- upper respiratory tract infections
- injection site reactions

- back pain
- nose bleeds

These are not all of the possible side effects of TEZSPIRE.

Call your doctor for medical advice about side effects. You may report side effects to FDA at 1‑800-FDA-1088.

General information about the safe and effective use of TEZSPIRE

Medicines are sometimes prescribed for purposes other than those listed in a Patient Information leaflet. Do not use TEZSPIRE for a condition for which it was not prescribed. Do not give TEZSPIRE to other people, even if they have the same symptoms that you have. It may harm them. You can ask your pharmacist or healthcare provider for information about TEZSPIRE that is written for health professionals.

What are the ingredients in TEZSPIRE?

Active ingredient: tezepelumab-ekko.

Inactive ingredients: glacial acetic acid, L-proline, polysorbate 80, sodium hydroxide, and water for injection.

Manufactured by:

AstraZeneca AB, Södertälje, Sweden SE-15185

US License No. 2059

At: Amgen Inc., One Amgen Center Drive, Thousand Oaks, CA 91320-1799

Marketed by: Amgen Inc. and AstraZeneca AB

©AstraZeneca and Amgen 2025

TEZSPIRE is a trademark of Amgen Inc. and AstraZeneca.

For more information, go to https://www.TEZSPIRE.com or call 1-800-236-9933.

This Patient Information has been approved by the U.S. Food and Drug Administration. Revised: October 2025

INSTRUCTIONS FOR USE

TEZSPIRE® (TEZ-SPY-ER)

(tezepelumab-ekko)

injection, for subcutaneous use

Single-dose Pre-filled pen

This Instructions for Use contains information on how to inject TEZSPIRE.

Before using your TEZSPIRE pre-filled pen, your healthcare provider should show you or your caregiver how to use it the right way.

Read this Instructions for Use before you start using your TEZSPIRE pre-filled pen and each time you get a refill. There may be new information. This information should not replace talking to your healthcare provider about your medical condition and your treatment.

If you or your caregiver have any questions, talk to your healthcare provider.

Important information you need to know before injecting TEZSPIRE

Store TEZSPIRE in a refrigerator between 36°F to 46°F (2°C to 8°C) in its original carton until you are ready to use it.

TEZSPIRE may be kept at room temperature between 68°F to 77˚F (20°C to 25°C) for a maximum of 30 days.

Store TEZSPIRE in the original carton to protect it from light.

When TEZSPIRE has reached room temperature, do not put it back in the refrigerator.

Throw away (dispose of) TEZSPIRE that has been stored at room temperature for more than 30 days.

Do not use your TEZSPIRE pre-filled pen if:

- it has been frozen
- it has been dropped or damaged
- the security seal on the carton has been broken
- the expiration date (EXP) has passed

Do not:

- freeze your pre-filled pen or expose it to heat
- shake your pre-filled pen
- share, or use your pre-filled pen more than 1 time

If any of the above happens, throw away the pre-filled pen in a puncture-resistant (sharps) container and use a new TEZSPIRE pre-filled pen.

Each TEZSPIRE pre-filled pen contains 1 dose of TEZSPIRE that can only be used 1 time.

TEZSPIRE is given only as an injection under the skin (subcutaneous).

Keep the TEZSPIRE pre-filled pen and all medicines out of the sight and reach of children.

Your TEZSPIRE pre-filled pen

Do not remove the cap until Step 6 of these instructions when you are ready to inject TEZSPIRE.

Preparing to inject TEZSPIRE

Step 1 – Gather supplies

  - 1 TEZSPIRE pre-filled pen from the refrigerator
  - 1 alcohol wipe
  - 1 cotton ball or gauze
  - 1 small bandage (optional)
  - 1 puncture-resistant (sharps) disposal container. See Step 10 for instructions on how to throw away (dispose of) the used TEZSPIRE pre-filled pen safely.

Step 2 – Prepare to use your TEZSPIRE pre-filled pen

Let TEZSPIRE come to room temperature between 68°F to 77˚F (20°C to 25°C) for about 60 minutes before giving the injection.

Keep the pre-filled pen in its original carton to protect it from light.

Do not warm the pre-filled pen in any other way. For example, do not warm it in a microwave or hot water, in direct sunlight, or near other heat sources.

Do not put TEZSPIRE back in the refrigerator after it has reached room temperature. Throw away (dispose of) TEZSPIRE that has been stored at room temperature for more than 30 days.

Do not remove the cap until Step 6.

Step 3 – Remove and check the pre-filled pen

Grab the middle of the pre-filled pen body to remove the pre-filled pen from its carton.

Check the pre-filled pen for damage. Do not use the pre-filled pen if the pre-filled pen is damaged.

Check the expiration date on the pre-filled pen. Do not use the pre-filled pen if the expiration date has passed.

Look at the liquid through the viewing window. The liquid should be clear and colorless to light yellow.

Do not inject TEZSPIRE if the liquid is cloudy, discolored, or contains large particles.

You may see small air bubbles in the liquid. This is normal. You do not need to do anything about it.

Injecting TEZSPIRE

Step 4 – Choose an injection site

If you are giving yourself the injection, the recommended injection site is the front of your thigh or the lower part of your stomach (abdomen). Do not inject yourself in the arm.

A caregiver may inject you in the upper arm, thigh, or abdomen.

For each injection, choose a different site that is at least 1 inch (3 cm) away from where you last injected.

Do not inject:

- into the 2‑inch (5 cm) area around your belly button
- where the skin is tender, bruised, scaly or hard
- into scars or damaged skin
- through clothing

Step 5 – Wash your hands and clean the injection site

Wash your hands well with soap and water.

Clean the injection site with an alcohol wipe in a circular motion. Let it air dry.

Do not touch the cleaned area before injecting.

Do not fan or blow on the cleaned area.

Step 6 – Pull off the cap

Do not remove the cap until you are ready to inject.

Hold the pre-filled pen body with 1 hand, and carefully pull the cap straight off with your other hand.

Put the cap to the side and throw it away later.

The orange needle guard is now exposed. The orange needle guard is there to prevent you from touching the needle.

Do not touch the needle or push on the orange needle guard with your finger.

Do not put the cap back on the pre-filled pen. You could cause the injection to happen too soon or damage the needle.

Step 7 – Inject TEZSPIRE

Follow your healthcare provider’s instruction on how to inject. You can either gently pinch the skin at the injection site or give the injection without pinching the skin.

Inject TEZSPIRE by following the steps in figures a, b, c and d.

When injecting, you will hear the first click that tells you the injection has started. Press and hold the pre-filled pen for 15 seconds until you hear the second click.

Do not change the position of the pre-filled pen after the injection has started.

Position the pre-filled pen.

- Place the orange needle guard flat against your skin (90-degree angle).
- Make sure you can see the viewing window.

Step 8 – Check the viewing window

Check the viewing window to make sure all the medicine has been injected.

If the orange plunger rod does not fill the viewing window, you may not have received the full dose.

If this happens or if you have any other concerns, contact your healthcare provider.

Step 9 – Check the injection site

There may be a small amount of blood or liquid where you injected. This is normal.

Gently hold pressure over your skin with a cotton ball or gauze until the bleeding stops.

Do not rub the injection site. If needed, cover the injection site with a small bandage.

Disposing of TEZSPIRE

Step 10 – Dispose of the used pre-filled pen safely

Each pre-filled pen contains a single dose of TEZSPIRE and cannot be used again. Do not put the cap back on the pre-filled pen.

Put your used pre-filled pen and cap in a sharps disposal container right away after use. Put other used supplies in your household trash.

Do not throw away the pre-filled pen in your household trash.

Throw away (Disposal) guidelines

If you do not have a FDA-cleared sharps disposal container, you may use a household container that is:

  - made of a heavy-duty plastic,
  - can be closed with a tight-fitting puncture-resistant lid, without sharps being able to come out,
  - upright and stable during use,
  - leak-resistant, and
  - properly labeled to warn of hazardous waste inside the container.

When your sharps disposal container is almost full, you will need to follow your community guidelines for the right way to dispose of your sharps disposal container. There may be state or local laws about how you should throw away used needles and syringes. For more information about safe sharps disposal, and for specific information about sharps disposal in the area that you live in, go to the FDA’s website at: http://www.fda.gov/safesharpsdisposal.

Do not dispose of your used sharps disposal container in your household trash unless your community guidelines permit this.

Do not recycle your used sharps disposal container.

Manufactured by:

AstraZeneca AB, Södertälje, Sweden SE-15185

US License No. 2059

At: Amgen Inc., One Amgen Center Drive, Thousand Oaks, CA 91320-1799

Marketed by: Amgen Inc. and AstraZeneca AB

©AstraZeneca and Amgen 2025

TEZSPIRE is a trademark of Amgen Inc. and AstraZeneca.

For more information, go to https://www.TEZSPIRE.com or call 1-800-236-9933.

This Instructions for Use has been approved by the U.S. Food and Drug Administration. Revised: October 2025

PACKAGE/LABEL PRINCIPAL DISPLAY PANEL

NDC 55513-100-01 Rx only

TEZSPIRETM

(tezepelumab-ekko)

Injection

210 mg/1.91 mL (110 mg/mL)

For Subcutaneous Injection Only

1 singe-dose vial. Discard unused portion.

AMGEN® AstraZeneca

PACKAGE/LABEL PRINCIPAL DISPLAY PANEL

NDC 55513-112-01

TEZSPIRETM (tezepelumab-ekko) Injection

210 mg/1.91 mL (110 mg/mL)

Rx Only

For Subcutaneous Injection Only

Store the pre-filled syringe refrigerated at 36° F to 46° F

(2° C to 8° C) in original carton to protect from light.

DO NOT SHAKE, FREEEZE, OR EXPOSE TO HEAT.

1 Singe-dose pre-filled syringe. Discard unused portion

AMGEN® AstraZeneca

PACKAGE/LABEL PRINCIPAL DISPLAY PANEL

NDC 55513-123-01 Rx only

TEZSPIRE®

(tezepelumab-ekko)

Injection

210 mg/1.91 mL (110 mg/mL)

For Subcutaneous Injection Only

Store the pre-filled pen refrigerated at 36°F to 46°F

(2°C to 8°C) in original carton to protect from light.

DO NOT SHAKE FREEZE OR EXPOSE TO HEAT.

1 Single-dose pre-filled pen.

Discard unused portion.

ATTENTION: Follow enclosed “Instructions for Use”

to prepare and deliver your dose.

AMGEN® AstraZeneca